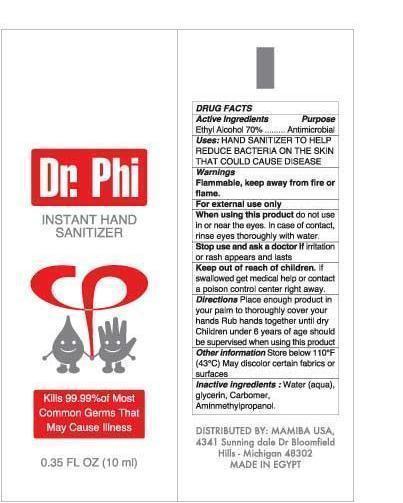 DRUG LABEL: Dr.Phi Instant Hand Sanitizer
NDC: 58161-155 | Form: GEL
Manufacturer: MAMIBA
Category: otc | Type: HUMAN OTC DRUG LABEL
Date: 20140902

ACTIVE INGREDIENTS: ALCOHOL 0.7 mL/1 mL
INACTIVE INGREDIENTS: WATER; CARBOMER 940; AMINOMETHYLPROPANOL

Dr.Phi Instant Hand Sanitizer

Active Ingredient

Ethyl Alcohol 70% V/V

Purpose

Antimicrobial

uses

HAND SANITIZER TO HELP REDUCE BACTERIA ON THE SKIN THAT COULD CAUSE DISEASE

uses

HAND SANITIZER TO HELP REDUCE BACTERIA ON THE SKIN THAT COULD CAUSE DISEASE

Warnings

Flammable, keep away from fire or flame.

For external use only

do not use in or near the eyes. In case of contact, rinse eyes thoroughly with water.

Stop use and ask a doctor

if irritation or rash appears and lasts

Keep out of reach of children

If swallowed get medical help or contact a poison control center right away.

Directions

Place enough product in your palm to thoroughly cover your hands Rub hands together until dry Children under 6 years of age should be supervised when using this product

other information

Store below 110°F (43°C)

May discolor certain fabrics or surfaces

inactive ingredients

Water (aqua), glycerin, Carbomer, Aminmethylpropanol